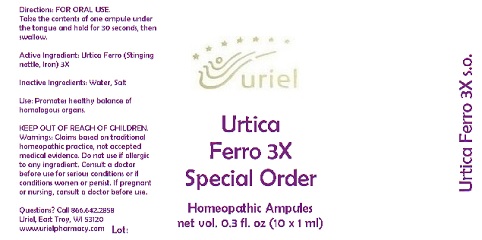 DRUG LABEL: Urtica Ferro 3 Special Order
NDC: 48951-9299 | Form: LIQUID
Manufacturer: Uriel Pharmacy Inc.
Category: homeopathic | Type: HUMAN OTC DRUG LABEL
Date: 20190430

ACTIVE INGREDIENTS: URTICA DIOICA 3 [hp_X]/1 mL; IRON 3 [hp_X]/1 mL
INACTIVE INGREDIENTS: WATER; SODIUM CHLORIDE

Urtica Ferro 3 Special Order

INDICATIONS AND USAGE

Directions: FOR ORAL USE.

DOSAGE AND ADMINISTRATION

Take the contents of one ampule under the tongue and hold for 30 seconds, then swallow.

Active Ingredient: Urtica Ferro (Stinging nettle, Iron) 3X

Inactive Ingredients: Water, Salt

PURPOSE

Use: Promotes healthy balance of homologous organs.

KEEP OUT OF REACH OF CHILDREN.

WARNINGS

Warnings: Claims based on traditional homeopathic practice, not accepted medical evidence. Do not use if allergic to any ingredient. Consult a doctor before use for serious conditions or if conditions worsen or persist. If pregnant or nursing, consult a doctor before use.

Questions? Call 866.642.2858
Uriel, East Troy, WI 53120
www.urielpharmacy.com